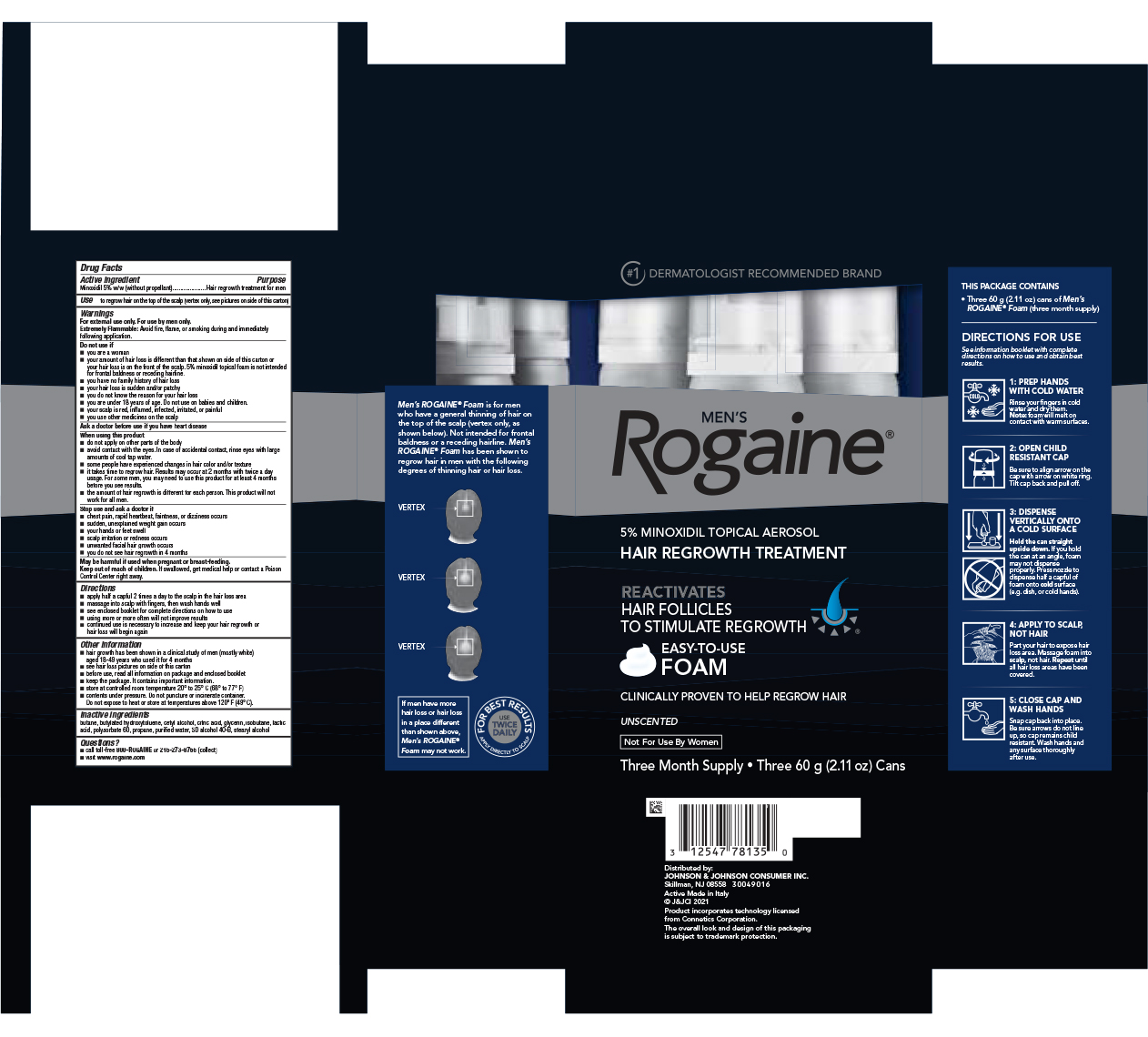 DRUG LABEL: Mens rogaine Minoxidil 

NDC: 69968-0031 | Form: AEROSOL, FOAM
Manufacturer: Kenvue Brands LLC
Category: otc | Type: HUMAN OTC DRUG LABEL
Date: 20241111

ACTIVE INGREDIENTS: MINOXIDIL 50 mg/1 g
INACTIVE INGREDIENTS: BUTANE; BUTYLATED HYDROXYTOLUENE; CETYL ALCOHOL; CITRIC ACID MONOHYDRATE; GLYCERIN; ISOBUTANE; LACTIC ACID, UNSPECIFIED FORM; POLYSORBATE 60; PROPANE; WATER; ALCOHOL; STEARYL ALCOHOL

MEN's Rogaine® UNSCENTED

Drug Facts

Active ingredient

Minoxidil 5% w/w (without propellant)

Purpose

Hair regrowth treatment for men

Use

to regrow hair on the top of the scalp (vertex only, see pictures on side of this carton)

Warnings

For external use only. For use by men only.

Extremely Flammable

Avoid fire, flame, or smoking during and immediately following application.

Do not Use if

- you are a woman
- your amount of hair loss is different than that shown on side of this carton or your hair loss is on the front of the scalp. 5% minoxidil topical foam is not intended for frontal baldness or receding hairline.
- you have no family history of hair loss
- your hair loss is sudden and/or patchy
- you do not know the reason for your hair loss
- you are under 18 years of age. Do not use on babies and children.
- your scalp is red, inflamed, infected, irritated, or painful
- you use other medicines on the scalp

Ask a doctor before use if you have heart disease

When using this product

- do not apply on other parts of the body
- avoid contact with the eyes. In case of accidental contact, rinse eyes with large amounts of cool tap water.
- some people have experienced changes in hair color and/or texture
- it takes time to regrow hair. Results may occur at 2 months with twice a day usage. For some men, you may need to use this product for at least 4 months before you see results.
- the amount of hair regrowth is different for each person. This product will not work for all men.

Stop use and ask a doctor if

- chest pain, rapid heartbeat, faintness, or dizziness occurs
- sudden, unexplained weight gain occurs
- your hands or feet swell
- scalp irritation or redness occurs
- unwanted facial hair growth occurs
- you do not see hair regrowth in 4 months

PREGNANCY OR BREAST FEEDING

May be harmful if used when pregnant or breast-feeding.

Keep out of reach of children. If swallowed, get medical help or contact a Poison Control Center right away.

Directions

- apply half a capful 2 times a day to the scalp in the hair loss area
- massage into scalp with fingers, then wash hands well
- see enclosed booklet for complete directions on how to use
- using more or more often will not improve results
- continued use is necessary to increase and keep your hair regrowth or hair loss will begin again

Other information

- hair growth has been shown in a clinical study of men (mostly white) aged 18-49 years who used it for 4 months
- see hair loss pictures on side of this carton
- before use, read all information on package and enclosed booklet
- keep the package. It contains important information
- store at controlled room temperature 20° to 25° C (68° to 77°F)
- contents under pressure. Do not puncture or incinerate container. Do not expose to heat or store at temperatures above 120°F (49°C).

Inactive ingredients

butane, butylated hydroxytoluene, cetyl alcohol, citric acid, glycerin, isobutane, lactic acid, polysorbate 60, propane, purified water, SD alcohol40-B, stearyl alcohol

Questions?

- call toll-free 800-ROGAINE or 215-273-8755 (collect)
- visit www.rogaine.com

Distributed by:
JOHNSON & JOHNSON CONSUMER INC.
Skillman, NJ 08558

PRINCIPAL DISPLAY PANEL - Three 60 g Can Package

#1 DERMATOLOGIST RECOMMENDED BRAND

MEN'S
Rogaine®

5% MINOXIDIL TOPICAL AEROSOL
HAIR REGROWTH TREATMENT

REACTIVATES
HAIR FOLLICLES

TO STIMULATE REGROWTH

EASY-TO-USE
FOAM

CLINICALLY PROVEN TO HELP REGROW HAIR

UNSCENTED

Not For Use By Women

Three Month Supply • Three 60 g (2.11 oz) Cans